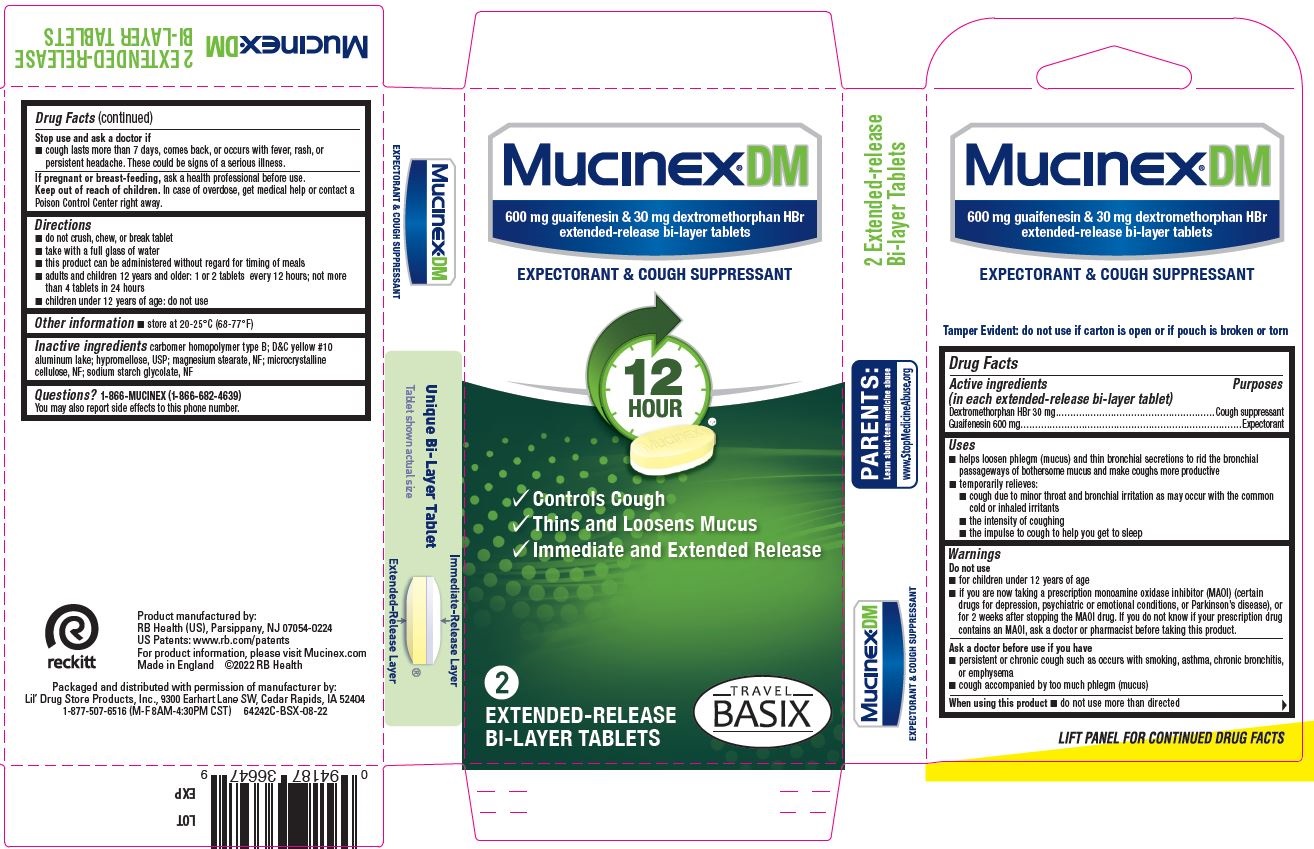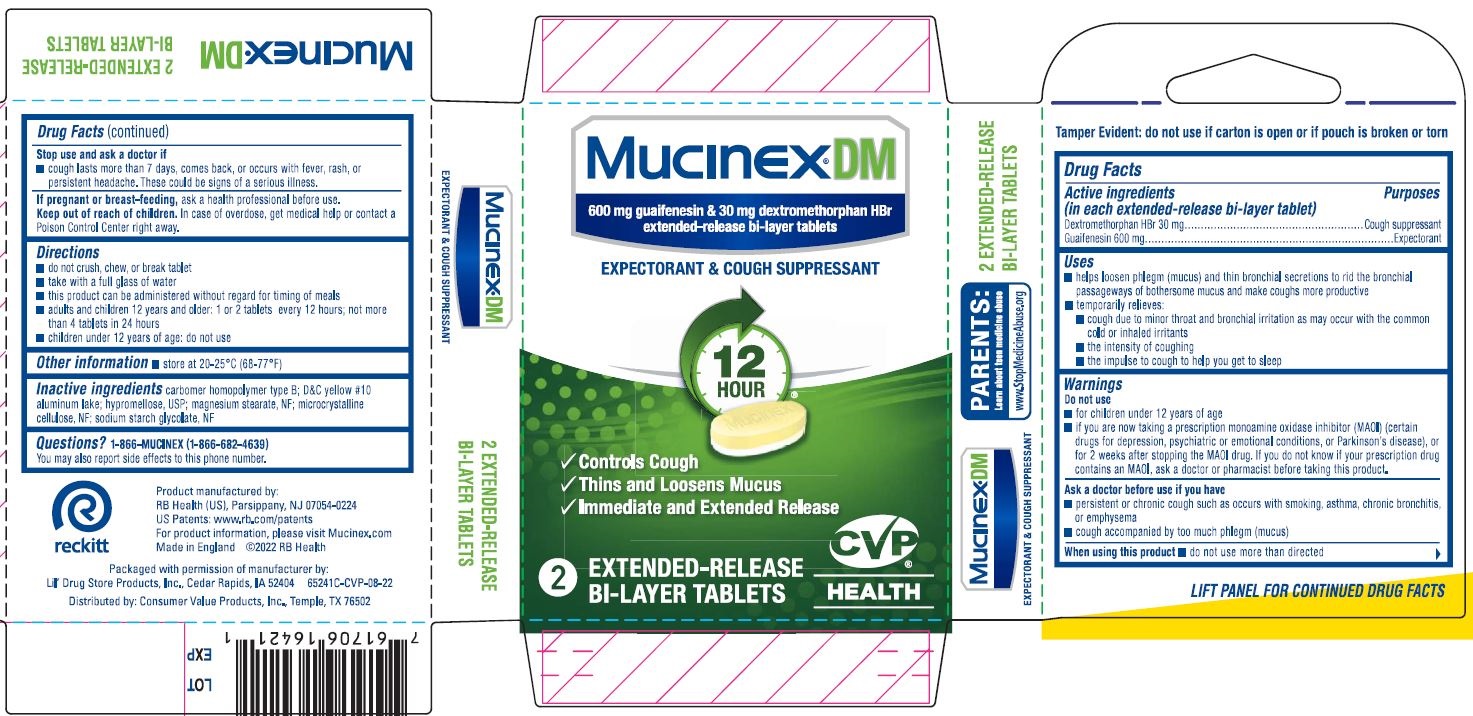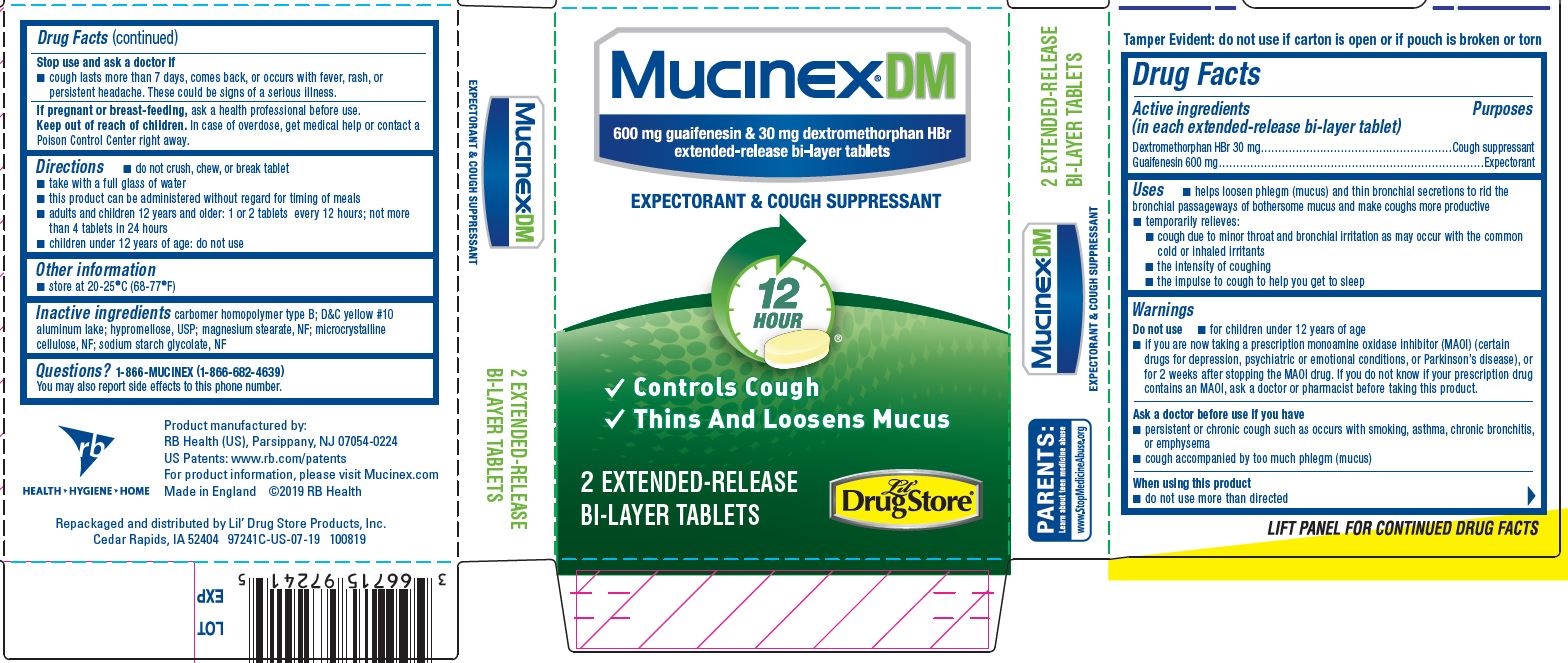 DRUG LABEL: Mucinex DM, CVP HEALTH
NDC: 66715-6524 | Form: TABLET, EXTENDED RELEASE
Manufacturer: Lil' Drug Store Products, Inc.
Category: otc | Type: HUMAN OTC DRUG LABEL
Date: 20231010

ACTIVE INGREDIENTS: GUAIFENESIN 600 mg/1 1; DEXTROMETHORPHAN HYDROBROMIDE 30 mg/1 1
INACTIVE INGREDIENTS: SODIUM STARCH GLYCOLATE TYPE A POTATO; CARBOMER HOMOPOLYMER TYPE B (ALLYL PENTAERYTHRITOL CROSSLINKED); D&C YELLOW NO. 10; ALUMINUM OXIDE; HYPROMELLOSE, UNSPECIFIED; MAGNESIUM STEARATE; MICROCRYSTALLINE CELLULOSE

Mucinex®DM
Lil' Drug Store®, TRAIL BASIX, CVP® HEALTH

Drug Facts

ACTIVE INGREDIENT

PURPOSE

Active ingredients (in each extended-release bi-layer tablet) | Purpose
Dextromethorphan HBr 30 mg | Cough suppressant
Guaifenesin 600 mg | Expectorant

Uses

- helps loosen phlegm (mucus) and thin bronchial secretions to rid the bronchial passageways of bothersome mucus and make coughs more productive
- temporarily relieves:
  - cough due to minor throat and bronchial irritation as may occur with the common cold or inhaled irritants
  - the intensity of coughing
  - the impulse to cough to help you get to sleep

Warnings

Do not use

- for children under 12 years of age
- if you are now taking a prescription monoamine oxidase inhibitor (MAOI) (certain drugs for depression, psychiatric or emotional conditions, or Parkinson's disease), or for 2 weeks after stopping the MAOI drug. If you do not know if your prescription drug contains an MAOI, ask a doctor or pharmacist before taking this product.

Ask a doctor before use if you have

- persistent or chronic cough such as occurs with smoking, asthma, chronic bronchitis, or emphysema
- cough accompanied by too much phlegm (mucus)

When using this product

- do not use more than directed

Stop use and ask a doctor if

- cough lasts more than 7 days, comes back, or occurs with fever, rash, or persistent headache. These could be signs of a serious illness.

PREGNANCY OR BREAST FEEDING

If pregnant or breast-feeding, ask a health professional before use.

Keep out of reach of children. In case of overdose, get medical help or contact a Poison Control Center right away.

Directions

- do not crush, chew, or break tablet
- take with a full glass of water
- this product can be administered without regard for timing of meals
- adults and children 12 years and older: 1 or 2 tablets every 12 hours; not more than 4 tablets in 24 hours
- children under 12 years of age: do not use

Other information

- store at 20-25°C (68-77°F)

Inactive ingredients

carbomer homopolymer type B; D&C yellow #10 aluminum lake; hypromellose, USP; magnesium stearate, NF; microcrystalline cellulose, NF; sodium starch glycolate, NF

Questions?

1-866-MUCINEX (1-866-682-4639)
You may also report side effects to this phone number.

Product manufactured by:
Reckitt Benckiser, Parsippany, NJ 07054-0224

Repackaged and distributed with permission of manufacturer by:
Lil' Drug Store Products, Inc., 1201 Continental Place NE, Cedar Rapids, IA 52402

Mucinex® DM 2ct, Lil' Drug Store® - PDP/Package

Mucinex® DM

600 mg guaifenesin & 30 mg dextromethorphan HBr

extended-release bi-layer tablets

EXPECTORANT & COUGH SUPPRESSANT

12 HOUR

[caplet image]

- Controls Cough
- Thins And Loosens Mucus

2 EXTENDED-RELEASE BI-LAYER TABLETS

[Lil' Drug Store® logo]

Mucinex® DM 2ct, TRAVEL BASIX - PDP/Package

Mucinex® DM

600 mg guaifenesin & 30 mg dextromethorphan HBr

extended-release bi-layer tablets

EXPEXTORANT & COUGH SUPPRESSANT

12

HOUR

[tablet image]

[check mark] Controls Cough

[check mark] Thins and Loosens Mucus

[check mark] Immediate and Extended release

2

EXTENDED-RELEASE

BI-LAYER TABLETS

[TRAVEL BASIX logo]

®

Mucinex® DM 2ct CVP® HEALTH - PDPPackage

Mucinex® DM

600 mg guaifenesin & 30 mg dextromethorphan HBr

extended-release bi-layer tablets

EXPEXTORANT & COUGH SUPPRESSANT

12

HOUR

[tablet image]

[check mark] Controls Cough

[check mark] Thins and Loosens Mucus

[check mark] Immediate and Extended release

2

EXTENDED-RELEASE

BI-LAYER TABLETS

[CVP® HEALTH logo]